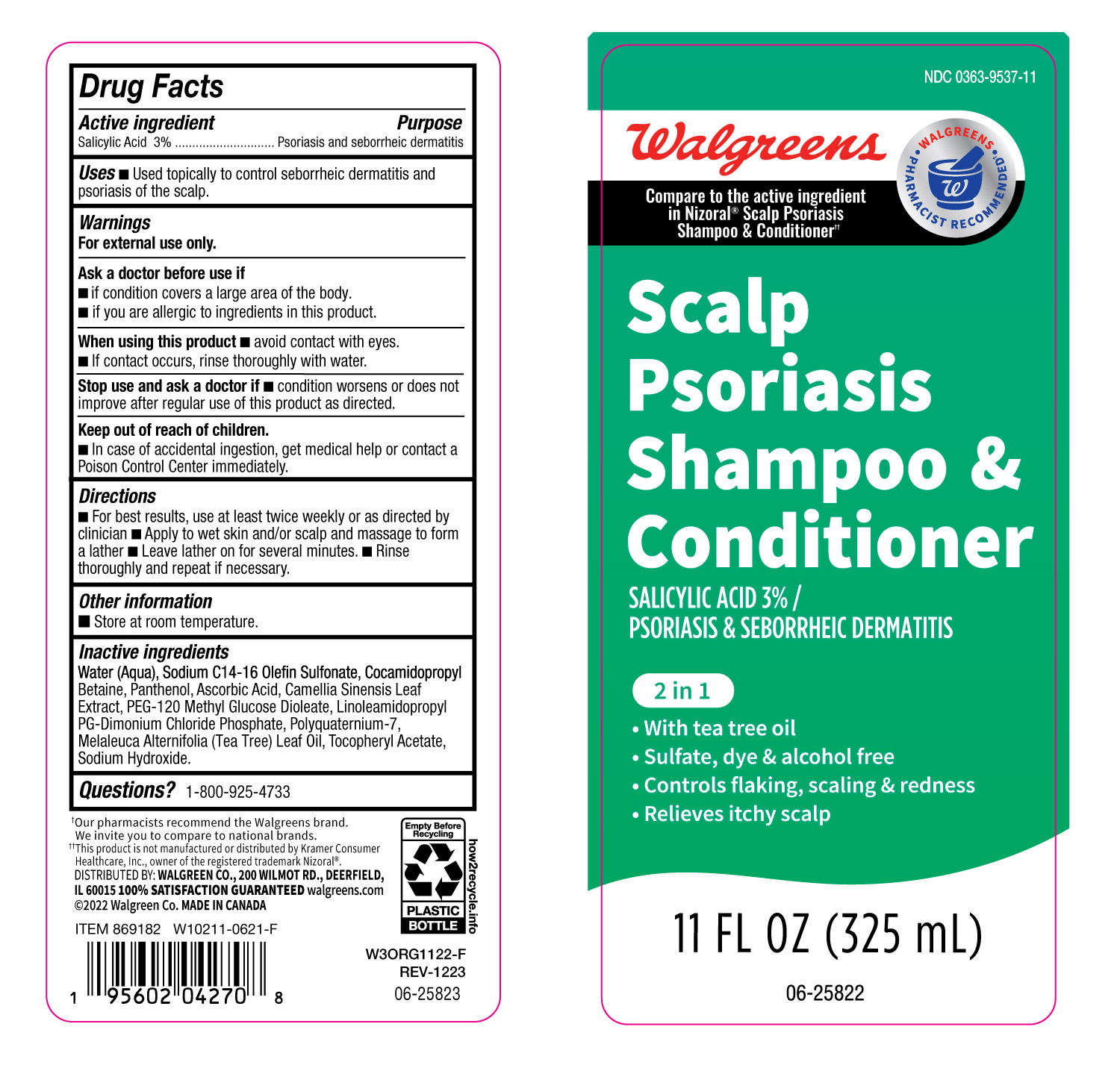 DRUG LABEL: Walgreens
NDC: 0363-9537 | Form: LOTION/SHAMPOO
Manufacturer: Walgreens
Category: otc | Type: HUMAN OTC DRUG LABEL
Date: 20250207

ACTIVE INGREDIENTS: SALICYLIC ACID 30 mg/1 mL
INACTIVE INGREDIENTS: SODIUM C14-16 OLEFIN SULFONATE; CAMELLIA SINENSIS LEAF; LINOLEAMIDOPROPYL PG-DIMONIUM CHLORIDE PHOSPHATE; SODIUM HYDROXIDE; ASCORBIC ACID; TEA TREE OIL; POLYQUATERNIUM-7 (70/30 ACRYLAMIDE/DADMAC; 900 KD); ALPHA-TOCOPHEROL ACETATE; COCAMIDOPROPYL BETAINE; PANTHENOL; PEG-120 METHYL GLUCOSE DIOLEATE; WATER

0363-9537-11- Walgreens Scalp Psoriasis shampoo

ACTIVE INGREDIENT

Salicylic Acid -3 %

Purpose

psoriasis and seborrheic dermatitis

Uses

Used topically to control seborrheic dermatitis and psoriasis of the scalp.

Warnings

For external use only

As a doctor before use if

- If condition covers a large area of the body.
- If you are allergic to ingredients in this product.

When using this product

- Avoid contact with eyes.
- If contact occurs, rinse thoroughly with water.

Stop use and ask a doctor if

- Condition worsens or does not improve after regular use of this product as directed.

Keep out of reach of children

- In case of accidental ingestion, get medical help or contact a Poison Control Center immediately.

Directions

- For best results, use at least twice weekly or as directed by clinician
- Apply to wet skin and/or scalp and massage to form a lather
- Leave lather on for several minutes.
- Rinse thoroughly and repeat if necessary.

Other information

- Store at room temperature

Inactive Ingredients

Water (Aqua), C 14-16 Olefin Sulfonate, Cocamidopropyl Betaine, Panthenol, Ascorbic Acid, Camellia Sinensis Leaf Extract, PEG-120 Methyl Glucose Dioleate, Linoleamidopropyl PG-Dimonium Chloride Phosphate, Polyquaternium-7, Melaleuca Aternifolia (Tea Tree) Leaf Oil, Tocopheryl Acetate, Sodium Hydroxide.

Questions???

1-800-925-4733